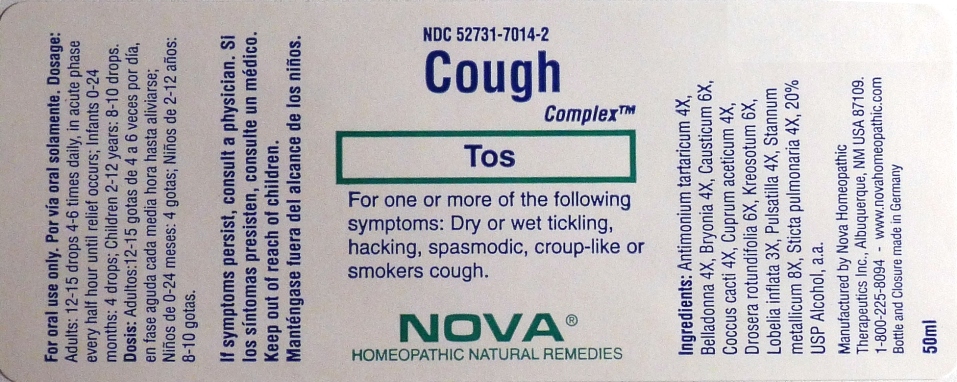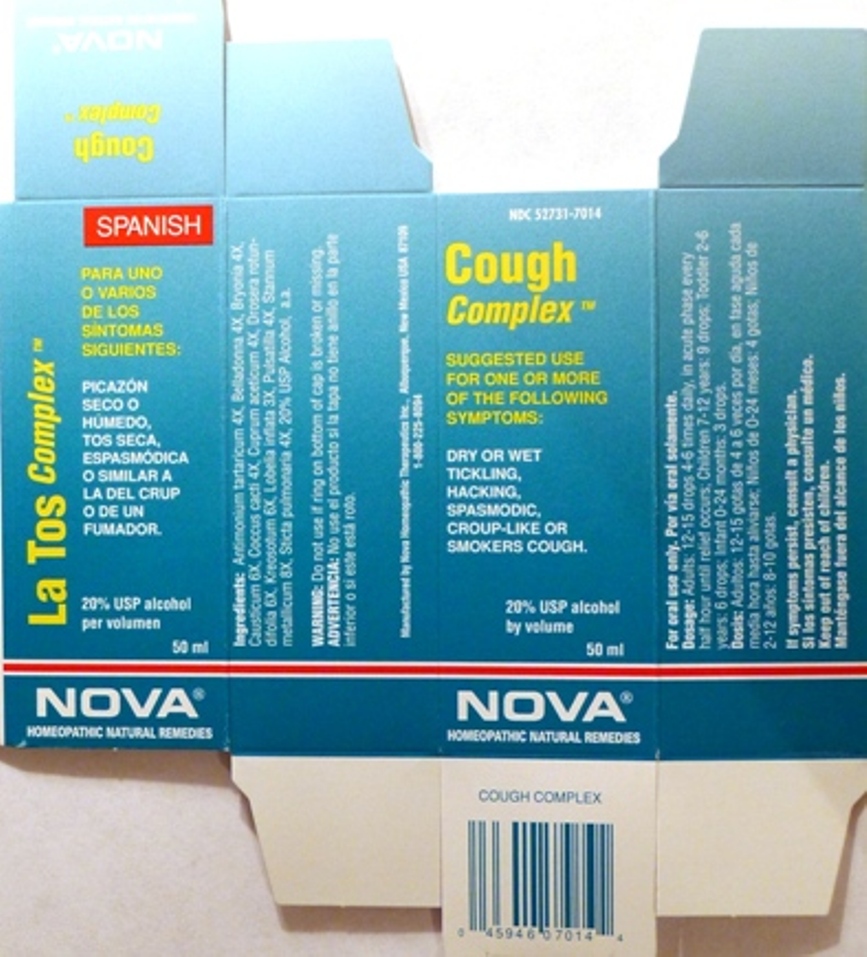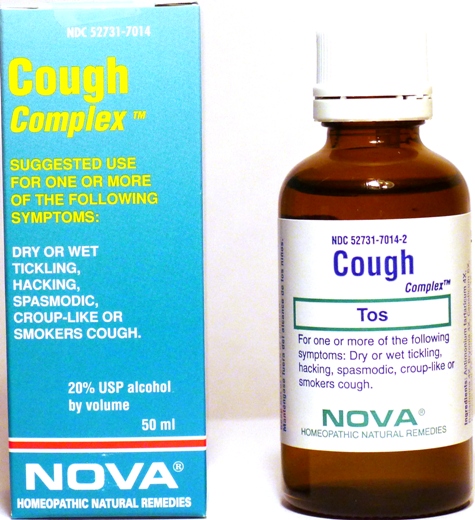 DRUG LABEL: Cough Complex
NDC: 52731-7014 | Form: LIQUID
Manufacturer: Nova Homeopathic Therapeutics, Inc.
Category: homeopathic | Type: HUMAN OTC DRUG LABEL
Date: 20110601

ACTIVE INGREDIENTS: ANTIMONY POTASSIUM TARTRATE 4 [hp_X]/1 mL; ATROPA BELLADONNA 4 [hp_X]/1 mL; BRYONIA ALBA ROOT 4 [hp_X]/1 mL; CAUSTICUM 6 [hp_X]/1 mL; PROTORTONIA CACTI 4 [hp_X]/1 mL; CUPRIC ACETATE 4 [hp_X]/1 mL; DROSERA ROTUNDIFOLIA 6 [hp_X]/1 mL; WOOD CREOSOTE 6 [hp_X]/1 mL; LOBELIA INFLATA 3 [hp_X]/1 mL; PULSATILLA VULGARIS 4 [hp_X]/1 mL; TIN 8 [hp_X]/1 mL; LOBARIA PULMONARIA 4 [hp_X]/1 mL
INACTIVE INGREDIENTS: ALCOHOL

Cough Complex

Purpose:

Suggested use for one or more of the following symptoms:

Dry or wet tickling,hacking,spasmodic,croup-like or smokers cough.

Usage and Dosage:

For oral use only.

DOSAGE AND ADMINISTRATION

Adults:
In Acute Phase:
12-15 drops, every half hour until relief occurs
When Relief Occurs:
12-15 drops, 4-6 times per day
Children 2-12 years:
8-10 drops, 4-6 times per day

Infants 0-24 months:
4 drops, 4-6 times per day

Warnings:

Keep out of reach of children.

WARNINGS

If symptoms persist, consult a physician.
Do not use if ring on bottom of cap is broken or missing.

Active Ingredients:

Antimonium tartaricum 4X, Belladonna 4X, Bryonia 4X,Causticum 6X, Coccus cacti 4X, Cuprum aceticum 4X, Drosera rotundifolia 6X, Kreosotum 6X, Lobelia inflata 3X, Pulsatilla 4X, Stannum metallicum 8X, Sticta pulmonaria 4X

Inactive Ingredients:

Alcohol, 20% USP

QUESTIONS

Manufactured by Nova Homeopathic Therapeutics Inc., Albuquerque, New Mexico USA 87109
1-800-225-8094

PACKAGE LABEL

Cough Complex Product

Cough Complex Bottle Label

Cough Complex Box